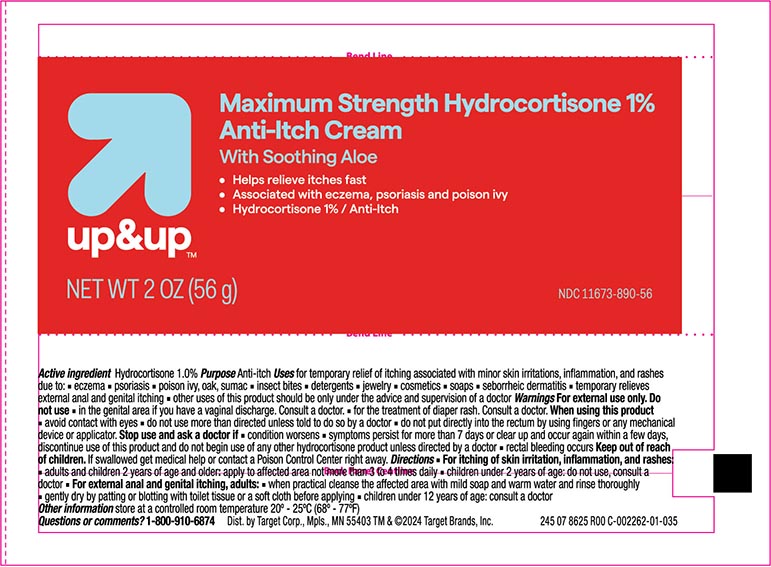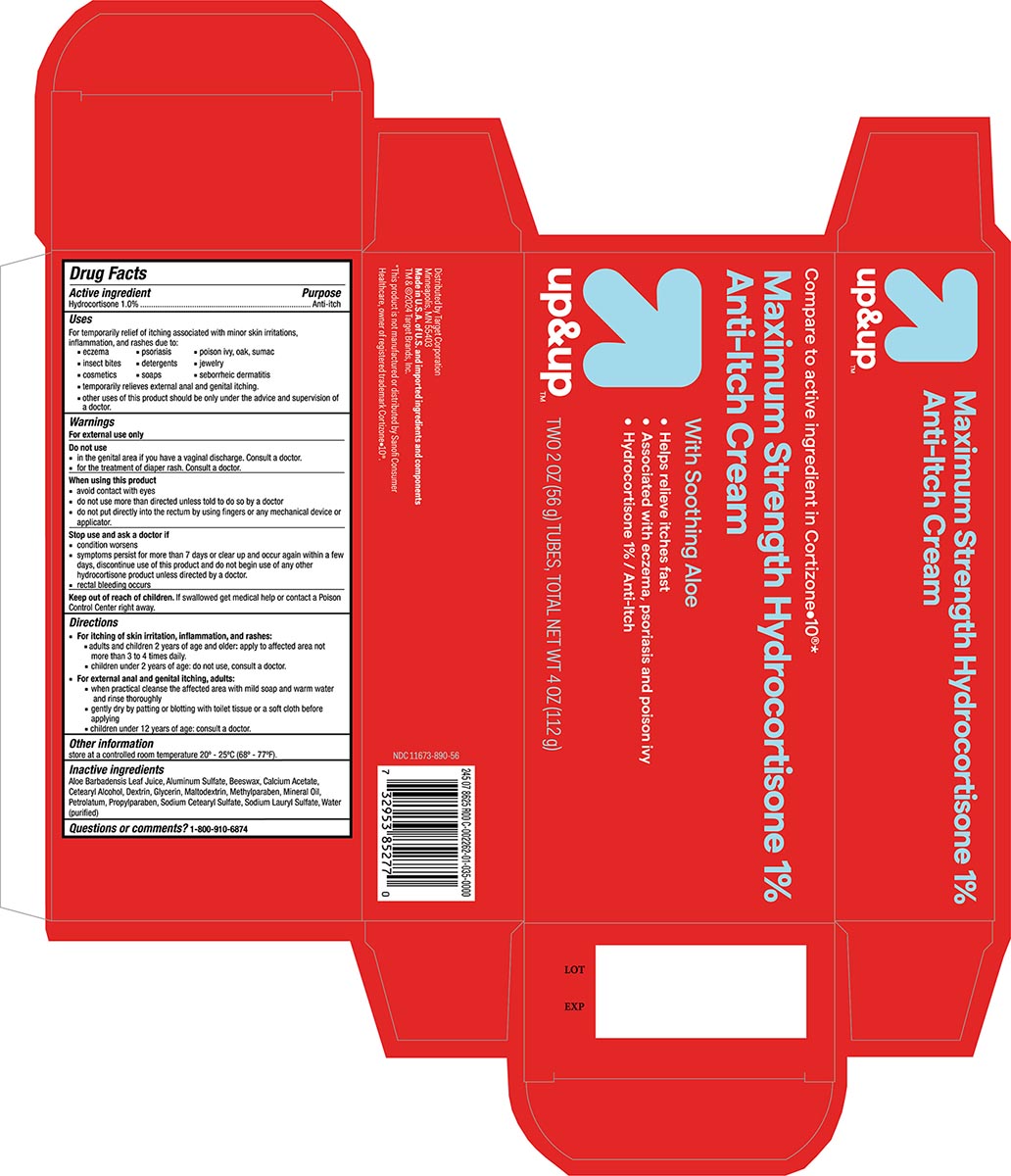 DRUG LABEL: Maximum Strength Hydrocortisone Anti-itch
NDC: 11673-890 | Form: CREAM
Manufacturer: Target Corporation
Category: otc | Type: HUMAN OTC DRUG LABEL
Date: 20240117

ACTIVE INGREDIENTS: HYDROCORTISONE 10 mg/1 g
INACTIVE INGREDIENTS: ALOE VERA LEAF; ALUMINUM SULFATE; YELLOW WAX; CALCIUM ACETATE; CETOSTEARYL ALCOHOL; ICODEXTRIN; GLYCERIN; MALTODEXTRIN; METHYLPARABEN; MINERAL OIL; PETROLATUM; PROPYLPARABEN; SODIUM CETOSTEARYL SULFATE; SODIUM LAURYL SULFATE; WATER

Target Up &Up Maximum Strength Hydrocortisone 1% Anti-itch Cream

Active Ingredient

Hydrocortisone 1.0%

Purpose

Anti-itch

Uses

For temporary relief of itching associated with minor skin irritations, inflammation, and rashes due to:

- eczema
- insect bites
- poison ivy
- poison oak
- poison sumac
- soaps
- detergents
- cosmetics
- jewelry
- seborrheic dermatitis
- psoriasis
- external feminine, genital and anal itching.
- Other uses of this product should be only under the advice and supervision of a doctor.

Warnings For external use only

Do not use

- for the treatment of diaper rash, consult a doctor.
- for external genital itching if you have a vaginal discharge, consult a doctor.

When using this product

- avoid contact with eyes
- do not use more than directed unless told ot do so by a doctor
- do not put this product into the rectum by using fingers or any mechanical device or applicator.

Stop use and ask a doctor if

- condition worsens
- symptoms persist for more than 7 days or clear up and occur again within a few days, discontinue use of this product and do not begin use of any other hydrocortisone product unless directed by a doctor.
- rectal bleeding occurs

Keep out of reach of children. If swallowed get medical help or contact a Poison Control Center right away.

Directions

For itching of skin irritation, inflammation, and rashes:

- ■ adults and children 2 years of age and older: apply to affected area not more than 3 to 4 times daily
- ■ children under 2 years of age: ask a doctor

For external anal and genital itching, adults:

- ■ when practical, clean the affected area with mild soap and warm water and rinse thoroughly
- ■ gently dry by patting or blotting with toilet tissue or a soft cloth before applying
- ■ apply to affected area not more than 3 to 4 times daily
- ■ children under 12 years of age: ask a doctor

Other information

store at a controlled room temperature 20 - 25ºC (68 - 77ºF).

Inactive Ingredients:

Aloe Barbadensis Leaf Juice, Aluminum Sulfate, Beeswax, Calcium Acetate, Cetearyl Alcohol, Dextrin, Glycerin, Maltodextrin, Methylparaben, Mineral Oil, Petrolatum, Propylparaben, Sodium Cetearyl Sulfate, Sodium Lauryl Sulfate, Purified Water

Principal Display Panel

Target Up&Up NDC 11673-890-56

Maxminium Strenght Hydrocortisone Cream

Hydrocortisone 1%

Anti-itch

NET WT 2OZ (56g)

TOTAL NET WT 4OZ (112g)